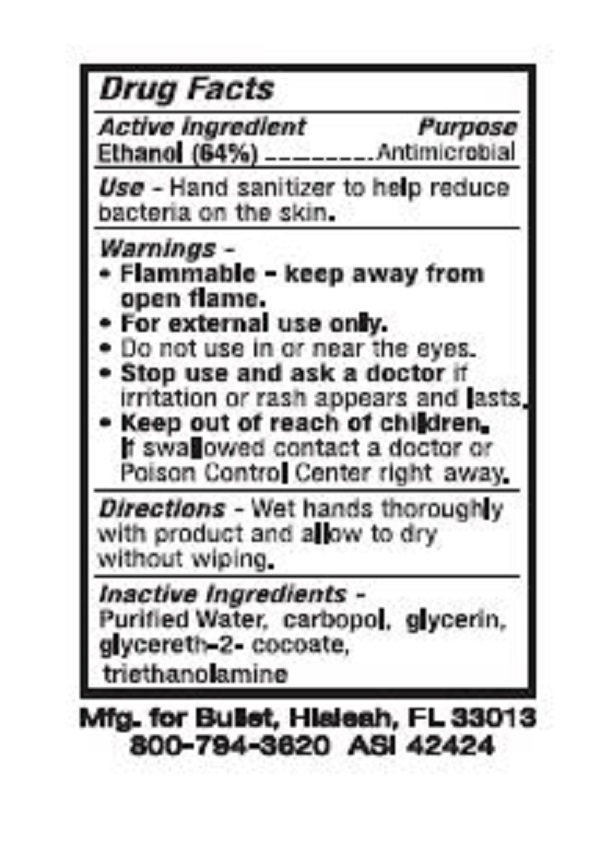 DRUG LABEL: Hand Sanitizer
NDC: 19392-210 | Form: LIQUID
Manufacturer: Bullet Line, LLC
Category: otc | Type: HUMAN OTC DRUG LABEL
Date: 20211217

ACTIVE INGREDIENTS: ALCOHOL 620 mL/1000 mL
INACTIVE INGREDIENTS: EDETOL; WATER; CARBOMER HOMOPOLYMER TYPE C (ALLYL PENTAERYTHRITOL CROSSLINKED)

Drug Facts

ACTIVE INGREDIENT

Ethyl Alcohol (64%)

PURPOSE

Antimicrobial

INDICATIONS AND USAGE

Hand sanitizer to help reduce bacteria on the skin

WARNINGS

Flammable - keep away from open flame.

For external use only.

Do not use in or near the eyes.

Stop use and ask doctor if irritation or rash appears and lasts.

Keep out of reach of children.

If swallowed, contact a doctor or Poison Control Center right away.

INACTIVE INGREDIENT

Purified Water, Carbopol, glycerin, glycereth-2-cocoate, triethanolamine

Keep out of reach of children. If swallowed, contact a doctor or Poison Control center right away.

DOSAGE AND ADMINISTRATION

Wet hands thoroughly with product and allow to dry without wiping.